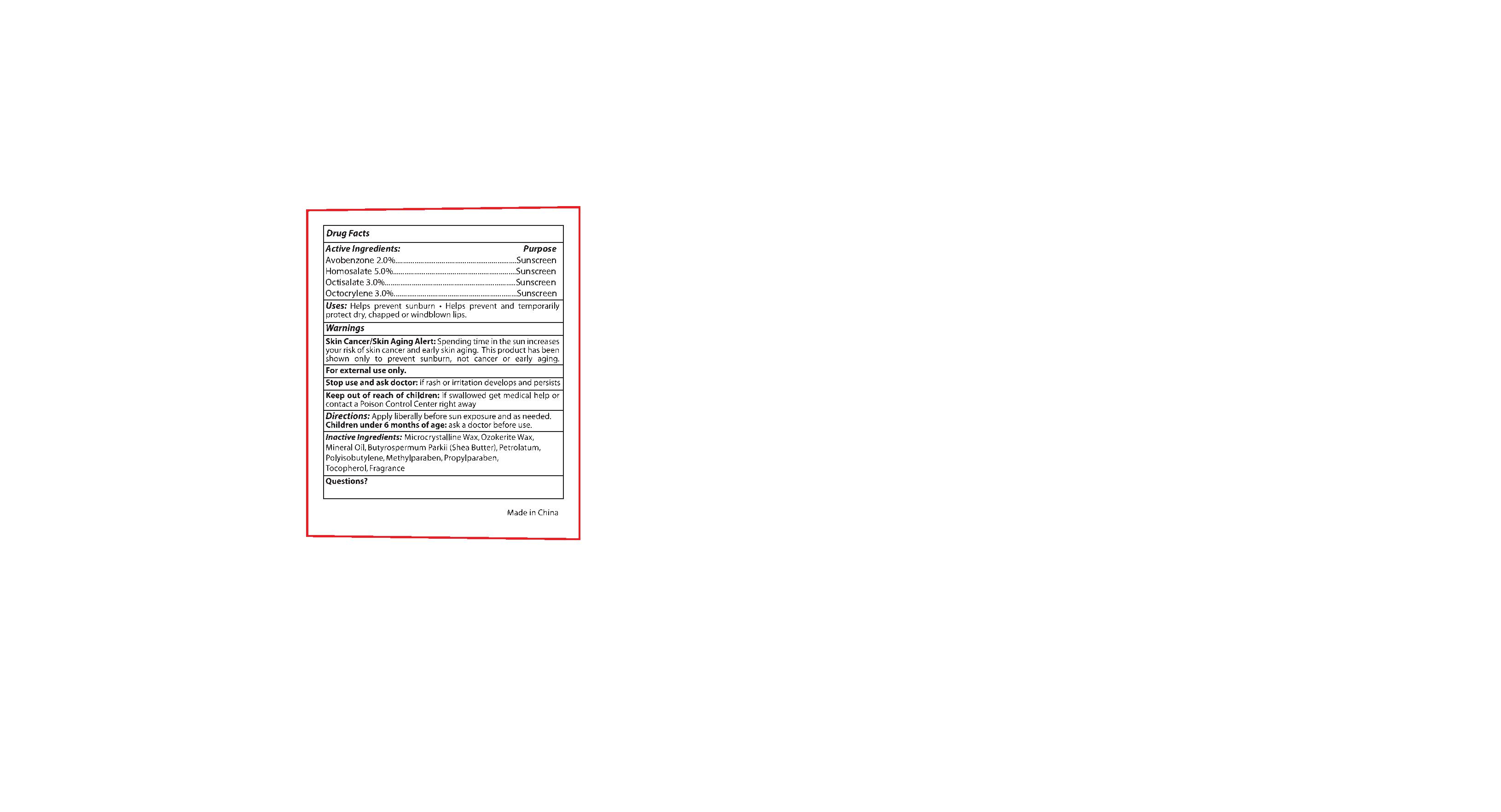 DRUG LABEL: lip balm SPF15( CB222)
NDC: 82953-041 | Form: LIPSTICK
Manufacturer: Cosmuses Cosmetics (Ningbo) Co., Ltd.
Category: otc | Type: HUMAN OTC DRUG LABEL
Date: 20250328

ACTIVE INGREDIENTS: OCTOCRYLENE 3 g/100 g; HOMOSALATE 5 g/100 g; AVOBENZONE 2 g/100 g; OCTISALATE 3 g/100 g
INACTIVE INGREDIENTS: PETROLATUM; TOCOPHEROL; MINERAL OIL; CERESIN; FRAGRANCE 13576; MICROCRYSTALLINE WAX; POLYISOBUTYLENE (1000 MW); BUTYROSPERMUM PARKII (SHEA) BUTTER; METHYLPARABEN; PROPYLPARABEN

Lip Balm SPF15 (CB222)

Drug Facts

Active ingredients

Avobenzone 2%

Homosalate 5%

Octisalate 3%

Octocrylene 3%

Purpose

Sunscreen

Uses

- Helps prevent sunburn
- helps prevent and temporarily protect dry, chapped or windblown lips.

Warnings

OTHER SAFETY INFORMATION

skin cancer/skin aging alert:

Spending time in the sun increases your risk of skin cancer and early skin aging. This product has been shown only to prevent sunburn , not cancer or early aging.

WARNINGS

For external use only

Stop use and ask a doctor if rash or irritation develops and persists

Keep out of reach of children. If swallowed, get medical help or contact a Poison Control Center right away.

Directions

- Apply liberally before sun exposure and as needed.
- Children under 6 months of age: Ask a doctor.

Inactive ingredients

Microcrystalline wax, Ozokerite wax, Mineral Oil, Butyrospermum Parkii (Shea) Butter, Petrolatum, Polyisobutene, Methylparaben, Propylparaben, Tocopherol, Fragrance

questions?